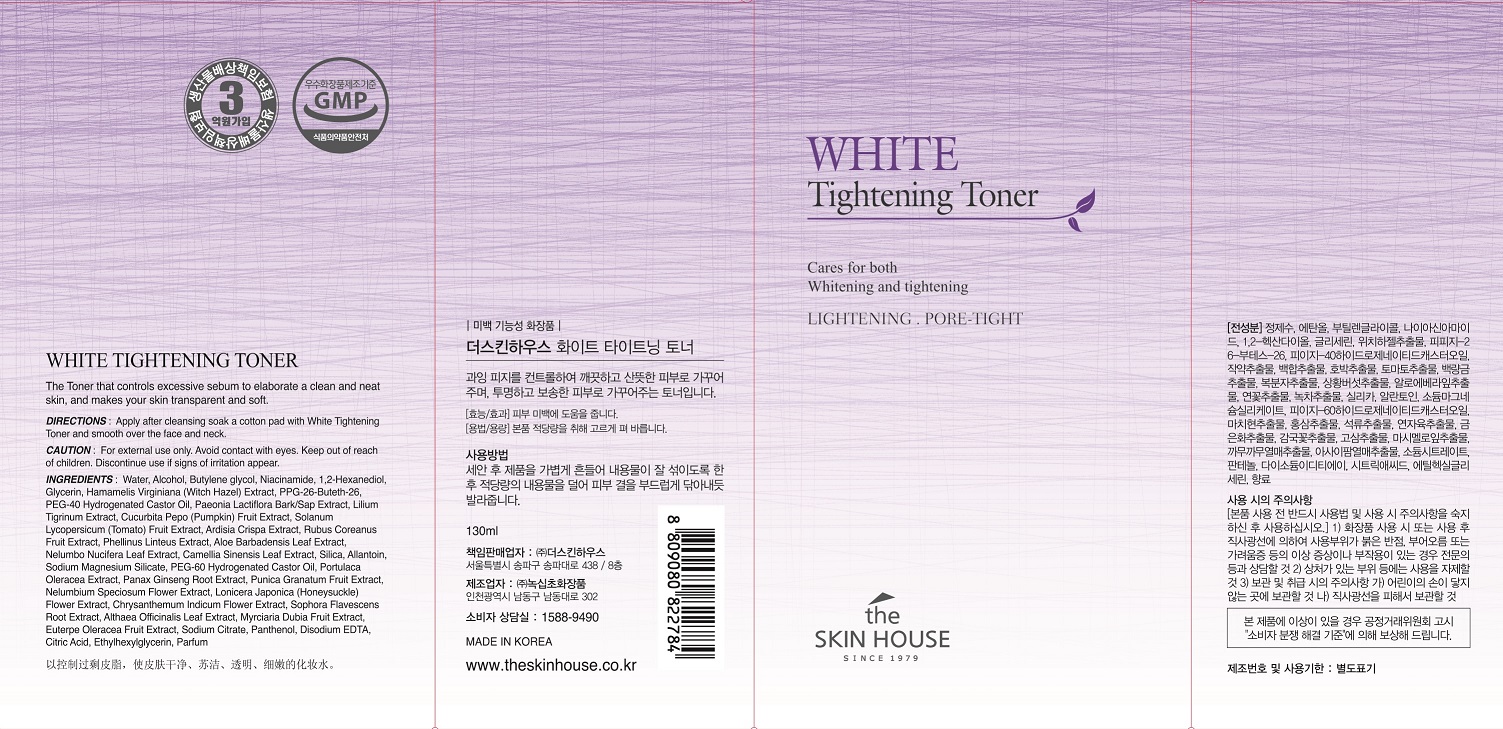 DRUG LABEL: THE SKINHOUSE WHITE TIGHTENING TONER
NDC: 73590-0004 | Form: LIQUID
Manufacturer: NOKSIBCHO cosmetic Co., Ltd.
Category: otc | Type: HUMAN OTC DRUG LABEL
Date: 20200129

ACTIVE INGREDIENTS: NIACINAMIDE 2 g/100 mL
INACTIVE INGREDIENTS: WATER; BUTYLENE GLYCOL

Drug Facts

ACTIVE INGREDIENT

Niacinamide, HamamelisVirginiana (Witch Hazel) Extract, PaeoniaLactiflora Bark/ Sap Extract, LiliumTigrinum Extract, ArdisiaCrispa Extract, Phellinus Linteus Extract, Camellia Sinensis Leaf Extract

INACTIVE INGREDIENT

Water
Alcohol
Butylene glycol
Niacinamide
1,2-Hexanediol
Glycerin
Hamamelis Virginiana (Witch Hazel) Extract
PPG-26-Buteth-26
PEG-40 Hydrogenated Castor Oil
Paeonia Lactiflora Bark/Sap Extract
Lilium Tigrinum Extract
Cucurbita Pepo (Pumpkin) Fruit Extract
Solanum Lycopersicum (Tomato) Fruit Extract
Ardisia Crispa Extract
Rubus Coreanus Fruit Extract
Phellinus Linteus Extract
Aloe Barbadensis Leaf Extract
Nelumbo Nucifera Leaf Extract
Camellia Sinensis Leaf Extract
Silica
Allantoin
Sodium Magnesium Silicate
PEG-60 Hydrogenated Castor Oil
Portulaca Oleracea Extract
Aloe Barbadensis Leaf Extract
Panax Ginseng Root Extract
Punica Granatum Fruit Extract
Paeonia Lactiflora Bark/Sap Extract
Lilium Tigrinum Extract
Nelumbium Speciosum Flower Extract
Lonicera Japonica (Honeysuckle) Flower Extract
Chrysanthemum Indicum Flower Extract
Cucurbita Pepo (Pumpkin) Fruit Extract
Solanum Lycopersicum (Tomato) Fruit Extract
Sophora Flavescens Root Extract
Althaea Officinalis Leaf Extract
Myrciaria Dubia Fruit Extract
Euterpe Oleracea Fruit Extract
Sodium Citrate
Panthenol
Disodium EDTA
Citric Acid
Ethylhexylglycerin
Parfum

PURPOSE

For those who want whitening products but not dry one.

It is a whitening pore care toner. It contains powder ingredients which control excessive sebum and brightens the skin tone through pore clean effect. This one toner has two effects which are whitening and pore tightening effects. It does not only tighten the pores, but also brightens the skin tone evenly to look shiny like ceramics with fresh feeling.

keep out of reach of the children

INDICATIONS AND USAGE

After cleansing, wet a cotton pad with enough toner and apply it on your face.

Apply it softly from the center part of your face to the outer part along the skin texture.

Pat your face to be absorbed completely.

WARNINGS

For external use only
When using this product

■ if the following symptoms occurs after use, stop use and consult with a skin specialist

red specks, swelling, itching

■ don’t use on the part where there is injury, eczema, or dermatitis

Keep out of reach of children

■ if swallowed, get medical help or contact a person control center immediately

DOSAGE AND ADMINISTRATION

for external use only